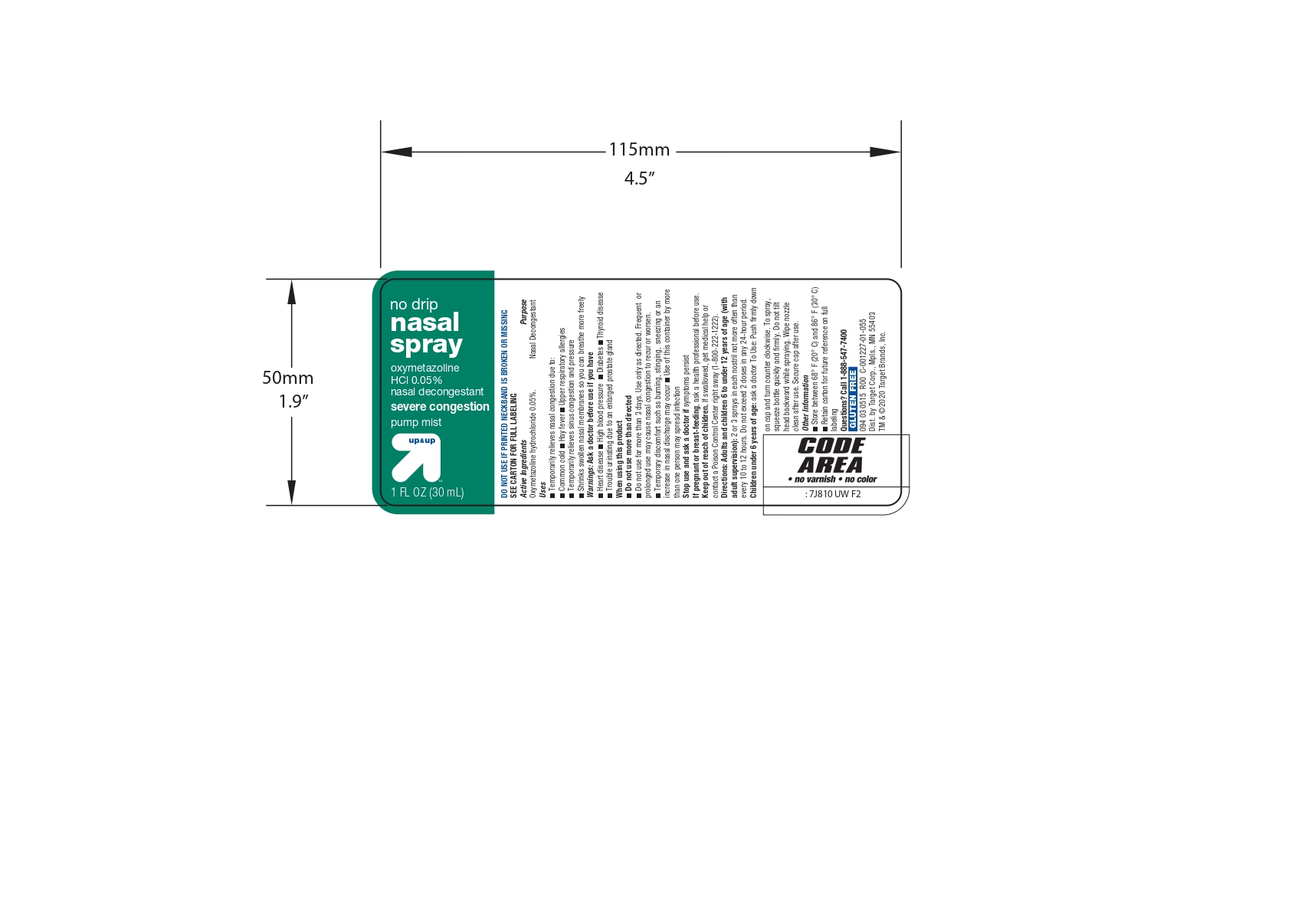 DRUG LABEL: No Drip
NDC: 13709-315 | Form: SPRAY
Manufacturer: NeilMed Pharmaceuticals Inc
Category: otc | Type: HUMAN OTC DRUG LABEL
Date: 20240111

ACTIVE INGREDIENTS: OXYMETAZOLINE HYDROCHLORIDE 15 mg/30 mL
INACTIVE INGREDIENTS: EDETATE DISODIUM; SODIUM BICARBONATE; PROPYLENE GLYCOL; WATER; SODIUM CHLORIDE; BENZALKONIUM CHLORIDE

No Drip Nasal Spray

Drug Facts : Active Ingredients

Oxymetazoline hydrochloride 0.05%.

Purpose

Nasal Decongestant

Uses

■ Temporarily relieves nasal congestion due to:
■ Common cold
■ Hay fever
■ Upper respiratory allergies
■ Temporarily relieves sinus congestion and
pressure
■ Shrinks swollen nasal membranes so you can
breathe more freely

Warnings

Ask a doctor before use if you have
■ Heart disease ■ High blood pressure
■ Diabetes ■ Thyroid disease
■ Trouble urinating due to an enlarged prostate
gland

When using this product

■ Do not use more than directed
■ Do not use for more than 3 days. Use only as
directed. Frequent or prolonged use may cause
nasal congestion to recur or worsen.
■ Temporary discomfort such as burning, stinging,
sneezing or an increase in nasal discharge may
occur
■ Use of this container by more than one person
may spread infection

Stop use and ask a doctor if symptoms persist

PREGNANCY

If pregnant or breast-feeding, ask a health professional before use.

Keep out of reach of children. If swallowed, get medical help or contact a Poison Control Center right away (1-800-222-1222).

Directions

■ Adults and children 6 to under 12 years of age (with adult supervision): 2 or 3 sprays in each nostril not more often than every 10 to 12 hours. Do not exceed 2 doses in any 24-hour period.
■ Children under 6 years of age: ask a doctor To Use: Push firmly down on cap and turn counter clockwise. To spray, squeeze bottle quickly and firmly. Do not tilt head backward while spraying. Wipe nozzle clean after use. Secure cap after use.

Other Information

■ Store between 68° F (20° C) and 86° F (30° C)
■ Retain carton for future reference on full labeling

Inactive ingredients

Sodium chloride, sodium bicarbonate, propylene glycol, edetate disodium, benzalkonium chloride, purified water.

How to use:

Hold white tabs, SQUEEZE grooved areaofcap FIRMLY and turn counter clockwise. Secure cap after use.

Directions
■ Adults and children 6 to under 12 years of age (with adult supervision): 2 or 3 sprays in each nostril not more often than every 10 to 12 hours. Do not exceed 2 doses in any 24-hour period.